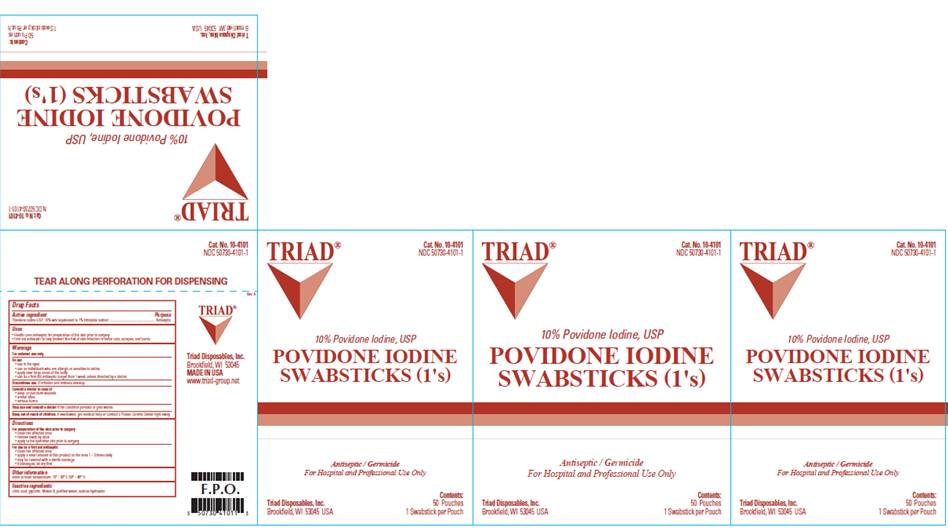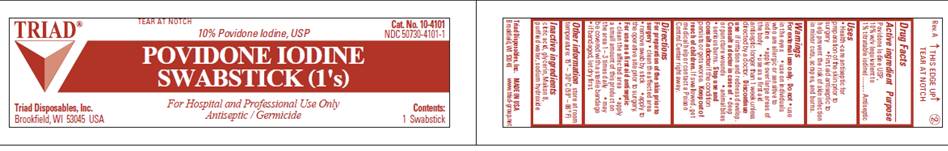 DRUG LABEL: Povidone-Iodine Prep Swabstick
NDC: 50730-4101 | Form: SOLUTION
Manufacturer: H and P Industries, Inc. dba Triad Group
Category: otc | Type: HUMAN OTC DRUG LABEL
Date: 20091125

ACTIVE INGREDIENTS: povidone-iodine .10 mg/1 mL
INACTIVE INGREDIENTS: citric acid monohydrate; glycerin; sodium hydroxide; water

DRUG FACTS

ACTIVE INGREDIENT

Povidone Iodine USP 10% w/v (equivalent to 1% titratable iodine)

PURPOSE

Antiseptic

USES

- Health Care Antiseptic for preparation of the skin prior to surgery

- First Aid Antiseptic to help prevent the risk of infection in minor cuts, scrapes and burns

WARNINGS

For external use only.

Do not

- use in the eyes
- apply over large areas of the body
- use on individuals who are allergic or sensitive to iodine
- use as a first aid antiseptic for longer than 1 week unless directed by a doctor

Ask a doctor in case of

- deep or puncture wounds
- animal bites
- serious burns

Stop use and ask a doctor

- if condition persists for more than 72 hours
- if irritation and redness develop

Keep out of reach of children

If swallowed, get medical help or contact a Poison Control Center right away.

DIRECTIONS

For preparation of the skin prior to surgery

- clean the affected area
- remove swab by stick
- apply to the operative site prior to surgery

As a first aid antiseptic

- clean the affected area
- apply a small amount of this product to the area 1-3 times daily
- may be covered with a sterile bandage
- if bandaged, let dry first

OTHER INFORMATION

Store at room temperature 15° - 30° C (59° - 86° F)

INACTIVE INGREDIENTS

citric acid, glycerin, Makon 8, purified water, sodium hydroxide

POUCH INFORMATION

TRIAD
Cat. No. 10-4101
NDC 50730-4101-1
10% Povidone Iodine, USP
POVIDONE IODINE
SWABSTICKS (1's)
Antiseptic / Germicide
For Hospital and Professional Use Only
Triad Disposables, Inc.
Brookfield, WI 53045 USA
Contents:
1 Swabstick

CARTON INFORMATION

TRIAD
Cat. No. 10-4101
NDC 50730-4101-1
10% Povidone Iodine, USP
POVIDONE IODINE
SWABSTICKS (1's)
Antiseptic / Germicide
For Hospital and Professional Use Only
Triad Disposables, Inc.
Brookfield, WI 53045 USA
Contents:
50 Pouches
1 Swabstick per Pouch